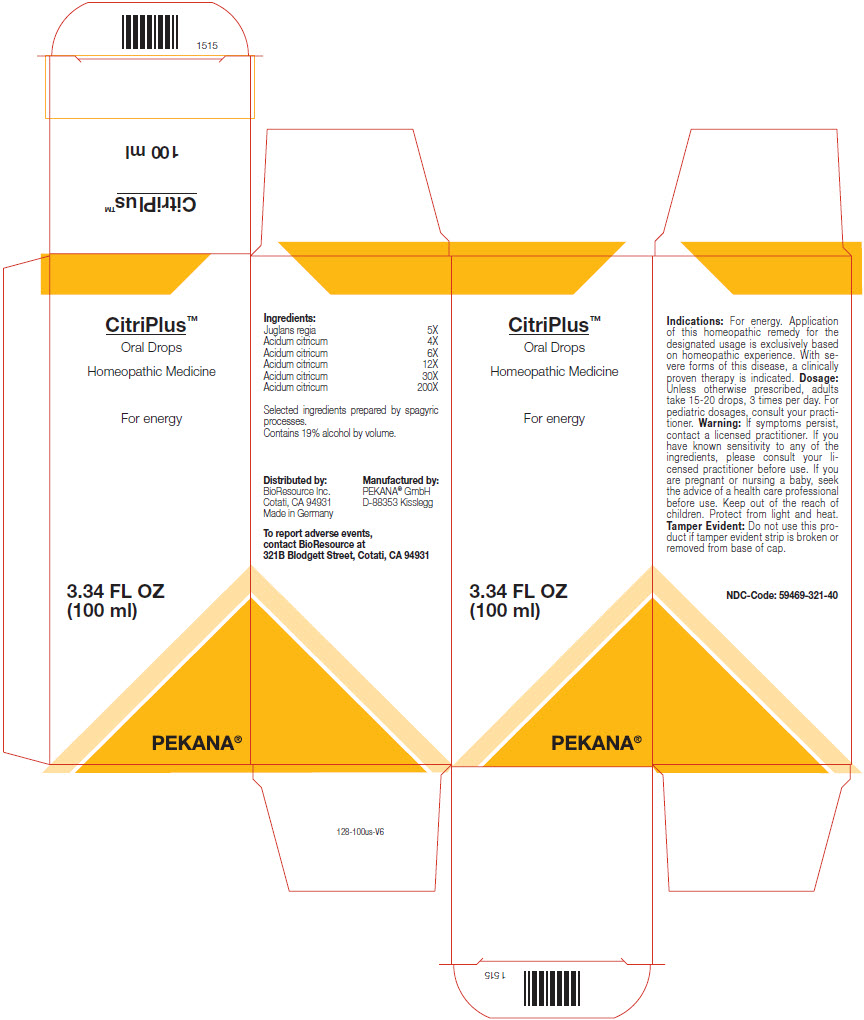 DRUG LABEL: CitriPlus
NDC: 59469-321 | Form: SOLUTION/ DROPS
Manufacturer: PEKANA Natuheilmittel GmbH
Category: homeopathic | Type: HUMAN OTC DRUG LABEL
Date: 20230111

ACTIVE INGREDIENTS: JUGLANS REGIA WHOLE 5 [hp_X]/100 mL; ANHYDROUS CITRIC ACID 4 [hp_X]/100 mL
INACTIVE INGREDIENTS: WATER; ALCOHOL

CitriPlus™

ACTIVE INGREDIENT

Ingredients:
Juglans regia | 5X
Acidum citricum | 4X
Acidum citricum | 6X
Acidum citricum | 12X
Acidum citricum | 30X
Acidum citricum | 200X

Selected ingredients prepared by spagyric processes.

INACTIVE INGREDIENT

Contains 19% alcohol by volume.

Indications

PURPOSE

For energy. Application of this homeopathic remedy for the designated usage is exclusively based on homeopathic experience. With severe forms of this disease, a clinically proven therapy is indicated.

Dosage

Unless otherwise prescribed, adults take 15-20 drops, 3 times per day. For pediatric dosages, consult your practitioner.

Warning

ASK DOCTOR

If symptoms persist, contact a licensed practitioner. If you have known sensitivity to any of the ingredients, please consult your licensed practitioner before use. If you are pregnant or nursing a baby, seek the advice of a health care professional before use.

Keep out of the reach of children.

STORAGE AND HANDLING

Protect from light and heat.

Tamper Evident

Do not use this product if tamper evident strip is broken or removed from base of cap.

QUESTIONS

To report adverse events, contact BioResource at 321B Blodgett Street, Cotati, CA 94931

Distributed by:
BioResource Inc.
Cotati, CA 94931

Manufactured by:
PEKANA® GmbH
D-88353 Kisslegg

PRINCIPAL DISPLAY PANEL - 100 ml Bottle Box

CitriPlus™

Oral Drops
Homeopathic Medicine

For energy

3.34 FL OZ
(100 ml)

PEKANA®